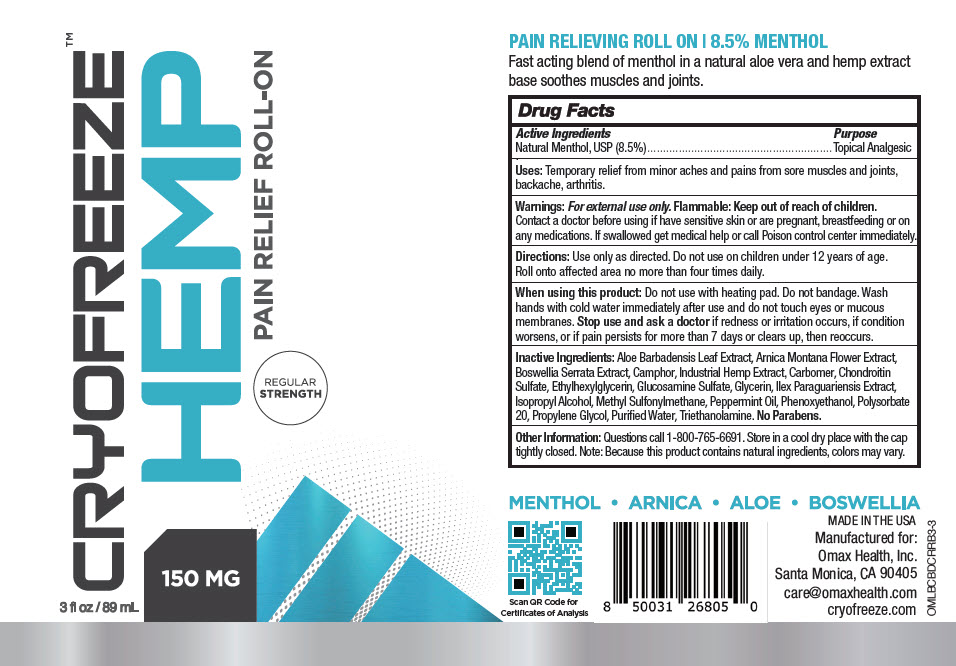 DRUG LABEL: Cryofreeze Roll-On Regular Strength
NDC: 73036-003 | Form: GEL
Manufacturer: Omax Health, Inc
Category: otc | Type: HUMAN OTC DRUG LABEL
Date: 20220318

ACTIVE INGREDIENTS: MENTHOL, UNSPECIFIED FORM 85 mg/1 mL
INACTIVE INGREDIENTS: ALOE VERA LEAF; ARNICA MONTANA WHOLE; INDIAN FRANKINCENSE; CAMPHOR (SYNTHETIC); HEMP; CARBOMER INTERPOLYMER TYPE A (ALLYL SUCROSE CROSSLINKED); CHONDROITIN SULFATE (SHARK); GLUCOSAMINE SULFATE POTASSIUM CHLORIDE; GLYCERIN; ILEX PARAGUARIENSIS LEAF; ISOPROPYL ALCOHOL; PHENOXYETHANOL; ETHYLHEXYLGLYCERIN; DIMETHYL SULFONE; PEPPERMINT OIL; POLYSORBATE 20; PROPYLENE GLYCOL; TROLAMINE; WATER

Cryofreeze™ Roll-On Regular Strength

Drug Facts

Active Ingredients

Natural Menthol, USP (8.5%)

Purpose

Topical Analgesic

Uses

Temporary relief from minor aches and pains from sore muscles and joints, backache, arthritis.

Warnings

For external use only.

Flammable: Keep out of reach of children.

Contact a doctor before using if have sensitive skin or are pregnant, breastfeeding or on any medications. If swallowed get medical help or call Poison control center immediately.

Directions

Use only as directed. Do not use on children under 12 years of age. Roll onto affected area no more than four times daily.

When using this product

Do not use with heating pad. Do not bandage. Wash hands with cold water immediately after use and do not touch eyes or mucous membranes. Stop use and ask a doctor if redness or irritation occurs, if condition worsens, or if pain persists for more than 7 days or clears up, then reoccurs.

Inactive Ingredients

Aloe Barbadensis Leaf Extract, Arnica Montana Flower Extract, Boswellia Serrata Extract, Camphor, Industrial Hemp Extract, Carbomer, Chondroitin Sulfate, Ethylhexylglycerin, Glucosamine Sulfate, Glycerin, Ilex Paraguariensis Extract, Isopropyl Alcohol, Methyl Sulfonylmethane, Peppermint Oil, Phenoxyethanol, Polysorbate 20, Propylene Glycol, Purified Water, Triethanolamine. No Parabens.

Other Information

Questions call 1-800-765-6691. Store in a cool dry place with the cap tightly closed. Note: Because this product contains natural ingredients, colors may vary.

PRINCIPAL DISPLAY PANEL - 89 mL Bottle Label

CRYOFREEZE™
HEMP
PAIN RELIEF ROLL-ON

REGULAR
STRENGTH

3 fl oz / 89 mL

150 MG